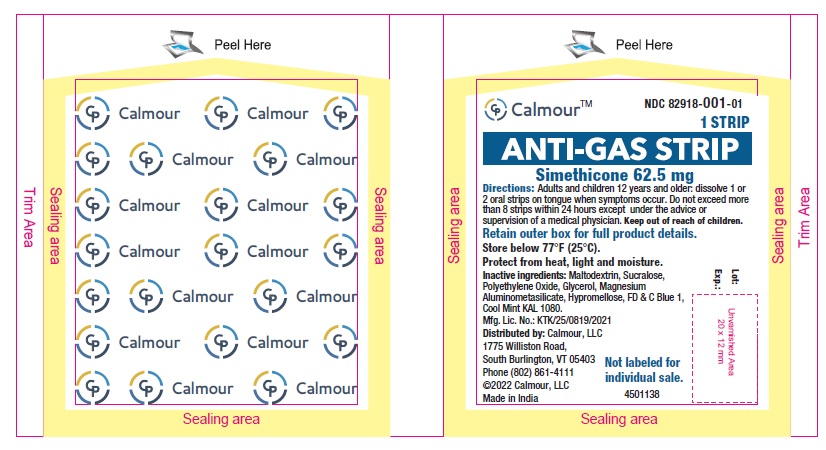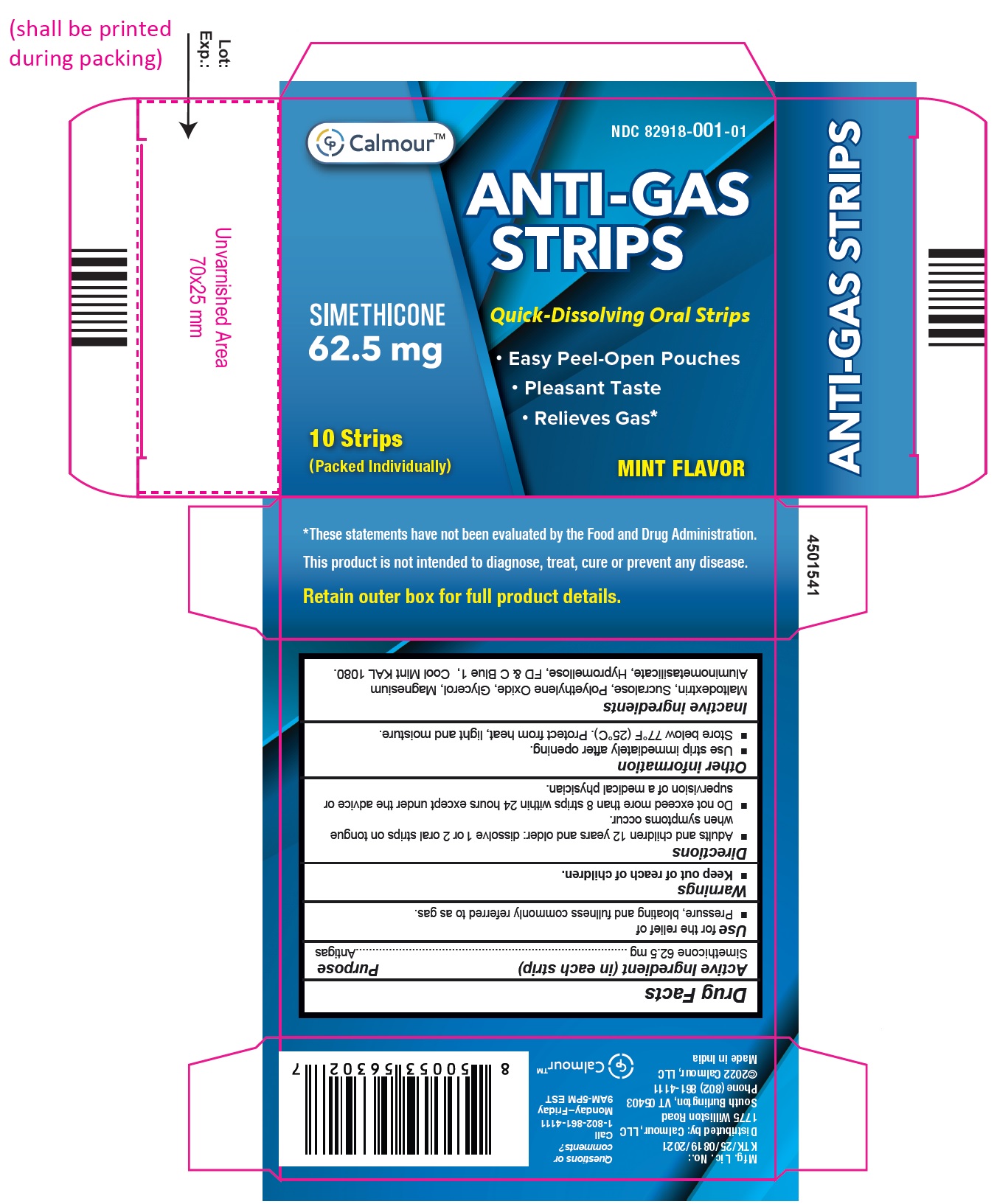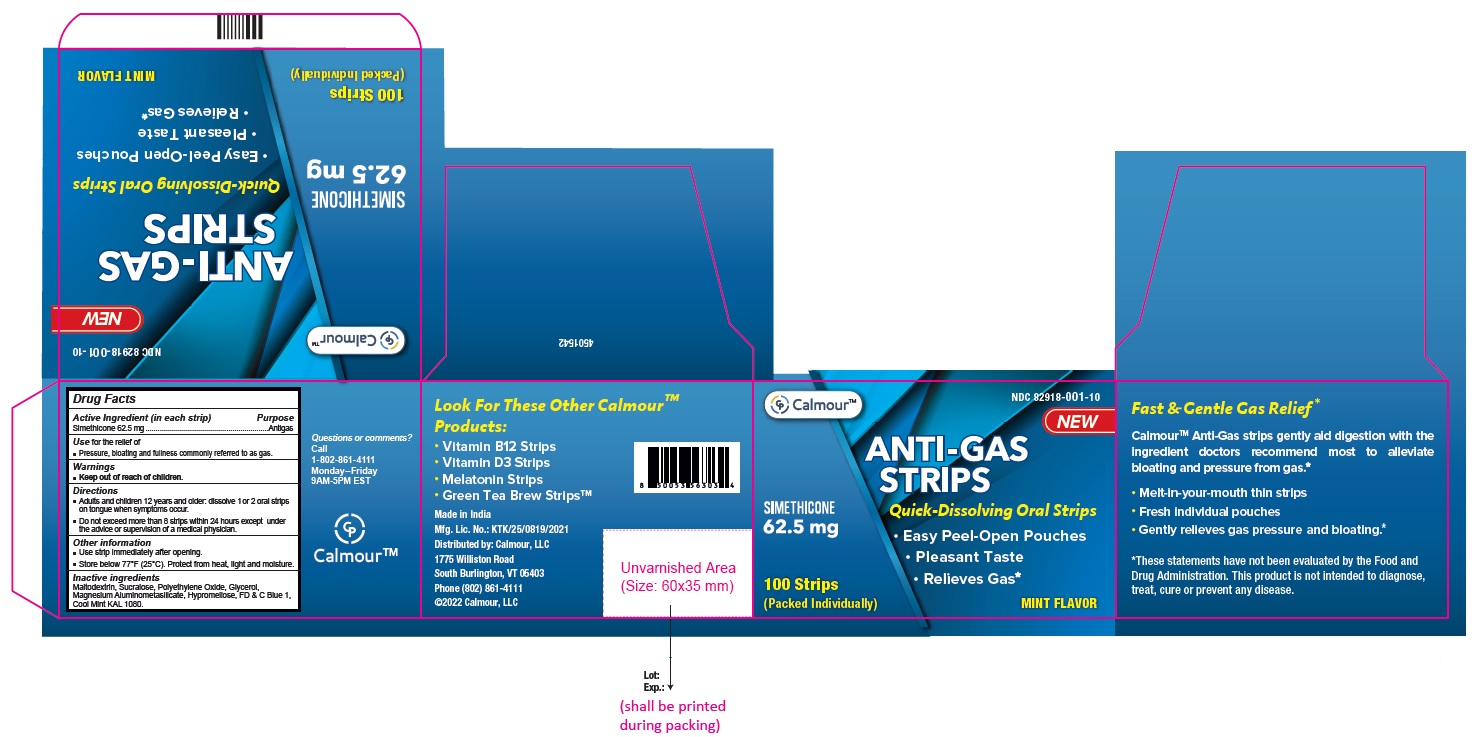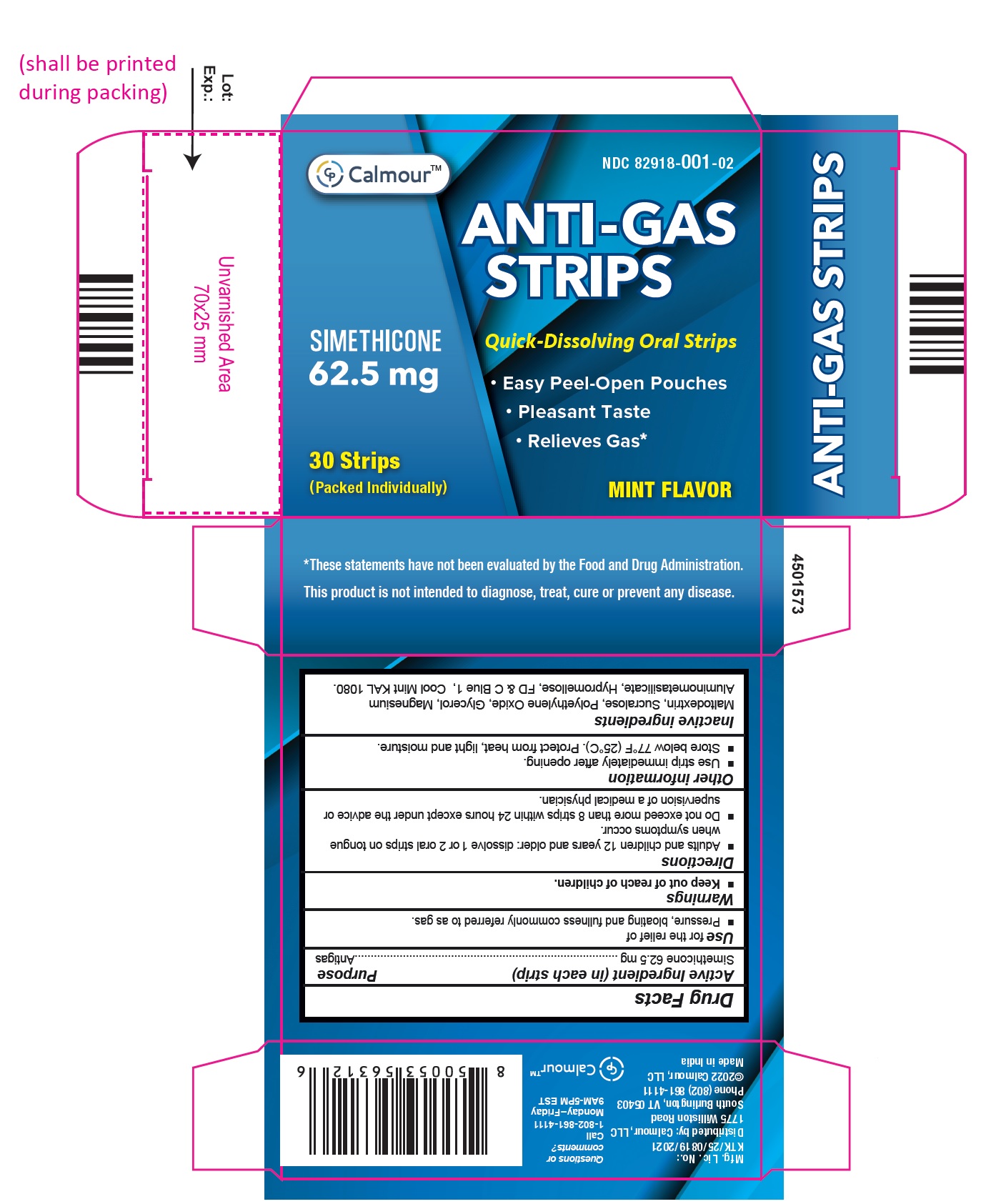 DRUG LABEL: Anti-Gas Strip
NDC: 82918-001 | Form: STRIP
Manufacturer: Calmour
Category: otc | Type: HUMAN OTC DRUG LABEL
Date: 20250109

ACTIVE INGREDIENTS: DIMETHICONE 62.5 mg/1 1
INACTIVE INGREDIENTS: MALTODEXTRIN; SUCRALOSE; POLYETHYLENE GLYCOL, UNSPECIFIED; GLYCERIN; SILODRATE; HYPROMELLOSE, UNSPECIFIED; FD&C BLUE NO. 1

Active Ingredient (in each strip)

Simethicone 62.5 mg

Purpose

Antigas

Use

For the relief of

- Pressure
- Bloating
- Fullness commonly referred to as gas.

Warnings

- Keep out of reach of children.

Directions

- Adults and children 12 years and older: dissolve 1 or 2 oral strips on tongue when symptoms occur.
- Do not exceed more than 8 strips within 24 hours except under the advice of supervision of a medical physician.

Other Information

- Use strip immediately after opening.
- Store below 77°F (25°C). Protect from heat, light and moisture.

Inactive Ingredients

Maltodextrin, Sucralose, Polyethylene Oxide, Glycerol, Magnesium Aluminometasilicate, Hypromellose, FD & C Blue 1, Cool Mint KAL 1080.

Questions or comments?

Call 1-802-861-4111

Monday-Friday

9AM-5PM EST

Distributed by:

Calmour, LLC

1775 Williston Road

South Burlington, VT 05403

Phone (802) 861-4111

©2022 Calmour, LLC

Made in India

PACKAGE LABEL.PRINCIPAL DISPLAY PANEL

POUCH LABEL

NDC 82918-001-01

ANTI-GAS STRIP

Simethicone 62.5 mg

1 STRIP

Pouch

INNER BOX

NDC 82918-001-01

ANTI-GAS STRIPS

Simethicone 62.5 mg

Quick Dissolving Oral Strips

• Easy Peel-Open Pouches

• Pleasant Taste

• Relieves Gas

MINT FLAVOR

10 Strips

(packed individually)

OUTER BOX

NDC 82918-001-10

ANTI-GAS STRIPS

Simethicone 62.5 mg

Quick Dissolving Oral Strips

• Easy Peel-Open Pouches

• Pleasant Taste

• Relieves Gas

MINT FLAVOR

100 Strips

(packed individually)

30's PACK CARTON

NDC 82918-001-02

ANTI-GAS STRIPS

Simethicone 62.5 mg

Quick Dissolving Oral Strips

• Easy Peel-Open Pouches

• Pleasant Taste

• Relieves Gas

MINT FLAVOR

30 Strips

(packed individually)